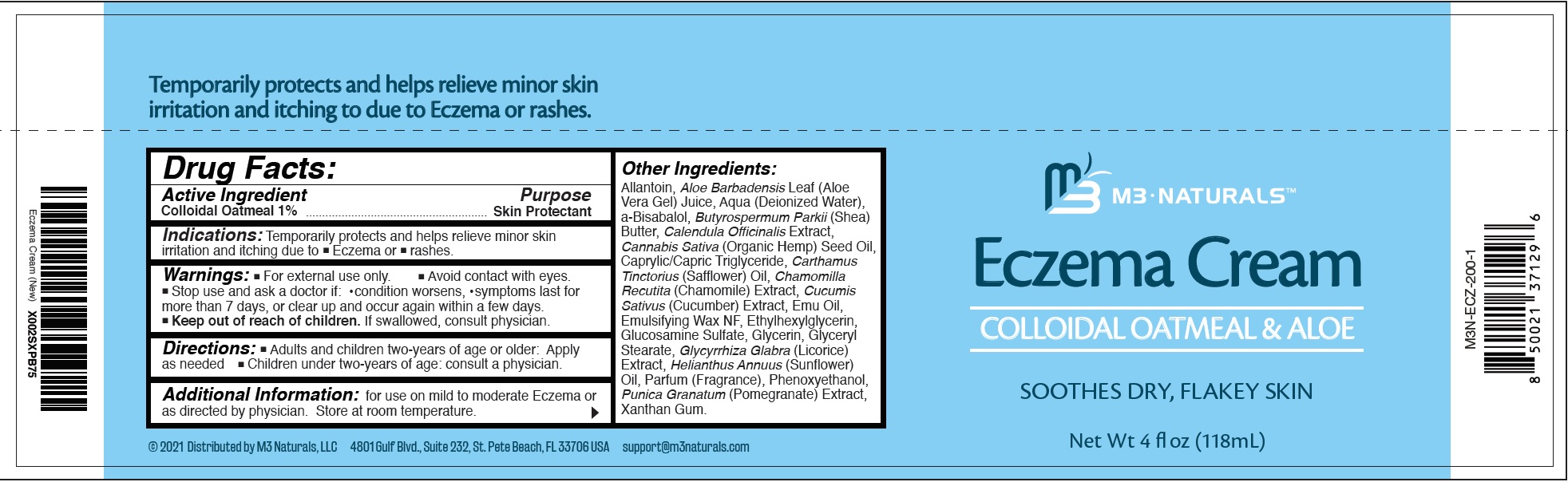 DRUG LABEL: M3 NATURALS Eczema Cream
NDC: 81985-186 | Form: CREAM
Manufacturer: M3 Naturals LLC
Category: otc | Type: HUMAN OTC DRUG LABEL
Date: 20231111

ACTIVE INGREDIENTS: OATMEAL 10 mg/1 mL
INACTIVE INGREDIENTS: ALLANTOIN; ALOE VERA LEAF; WATER; SHEA BUTTER; CALENDULA OFFICINALIS FLOWER; CANNABIS SATIVA SEED OIL; MEDIUM-CHAIN TRIGLYCERIDES; CARTHAMUS TINCTORIUS FLOWER OIL; CHAMOMILE; CUCUMBER; EMU OIL; ETHYLHEXYLGLYCERIN; GLUCOSAMINE SULFATE; GLYCERIN; GLYCERYL MONOSTEARATE; LICORICE; HELIANTHUS ANNUUS FLOWERING TOP; PHENOXYETHANOL; POMEGRANATE; XANTHAN GUM

M3 NATURALS: Eczema Cream

Active Ingredient

Colloidal Oatmeal 1%

Purpose

Skin Protectant

Indications:

Temporarily protects and helps relieve minor skin irritation and itching due to ■ Eczema or ■ rashes.

Warnings:

■ For external use only. ■ Avoid contact with eyes.

Stop use and ask a doctor if:

- condition worsens,
- symptoms last for more than 7 days, or clear up and occur again within a few days.

Keep out of reach of children.

- If swallowed, consult physician.

Directions:

- Adults and children two-years of age or older: Apply as needed
- Children under two-years of age: consult a physician.

Additional Information:

for use on mild to moderate Eczema or as directed by physician. Store at room temperature.

Other Ingredients:

Allantoin, Aloe Barbadensis Leaf (Aloe Vera Gel) Juice, Aqua (Deionized Water), a-Bisabalol, Butyrospermum Parkii (Shea) Butter, Calendula Officinalis Extract, Cannabis Sativa (Organic Hemp) Seed Oil, Caprylic/Capric Triglyceride, Carthamus Tinctorius (Safflower) Oil, Chamomilla Recutita (Chamomile) Extract, Cucumis Sativus (Cucumber) Extract, Emu Oil, Emulsifying Wax NF, Ethylhexylglycerin, Glucosamine Sulfate, Glycerin, Glyceryl Stearate, Glycyrrhiza Glabra (Licorice) Extract, Helianthus Annuus (Sunflower) Oil, Parfum (Fragrance), Phenoxyethanol, Punica Granatum (Pomegranate) Extract, Xanthan Gum.